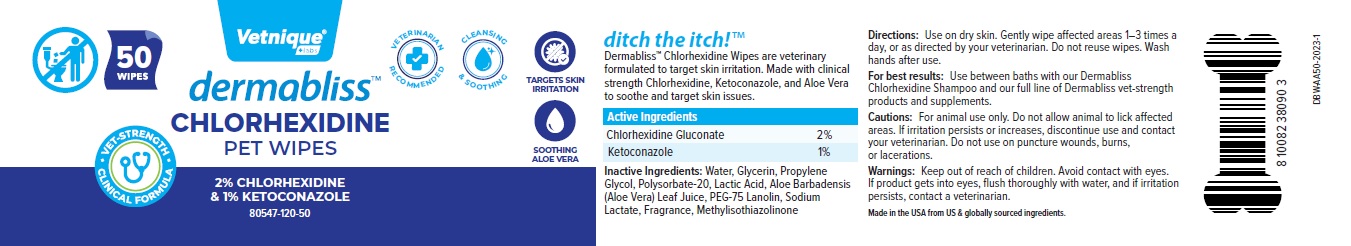 DRUG LABEL: dermabliss PET WIPES
NDC: 80547-120 | Form: CLOTH
Manufacturer: Vetnique Labs LLC
Category: animal | Type: OTC ANIMAL DRUG LABEL
Date: 20230810

ACTIVE INGREDIENTS: CHLORHEXIDINE GLUCONATE 20 mg/1 mL; KETOCONAZOLE 10 mg/1 mL
INACTIVE INGREDIENTS: WATER; GLYCERIN; PROPYLENE GLYCOL; POLYSORBATE 20; LACTIC ACID, UNSPECIFIED FORM; ALOE VERA LEAF; PEG-75 LANOLIN; SODIUM LACTATE; METHYLISOTHIAZOLINONE

dermabliss™ CHLORHEXIDINE PET WIPES

Active Ingredients

Chlorhexidine Gluconate 2%
Ketoconazole 1%

INDICATIONS AND USAGE

Dermabliss™ Chlorhexidine Wipes are veterinary formulated to target skin irritation. Made with clinical strength Chlorhexidine, Ketoconazole, and Aloe Vera to soothe and target skin issues.

INACTIVE INGREDIENT

Inactive Ingredients: Water, Glycerin, Propylene Glycol, Polysorbate-20, Lactic Acid, Aloe Barbadensis (Aloe Vera) Leaf Juice, PEG-75 Lanolin, Sodium Lactate, Fragrance, Methylisothiazolinone

DOSAGE AND ADMINISTRATION

Directions: Use on dry skin. Gently wipe affected areas 1–3 times a day, or as directed by your veterinarian. Do not reuse wipes. Wash hands after use.

For best results: Use between baths with our Dermabliss Chlorhexidine Shampoo and our full line of Dermabliss vet-strength products and supplements.

PRECAUTIONS

Cautions: For animal use only. Do not allow animal to lick affected areas. If irritation persists or increases, discontinue use and contact your veterinarian. Do not use on puncture wounds, burns, or lacerations.

WARNINGS

Warnings: Keep out of reach of children. Avoid contact with eyes. If product gets into eyes, flush thoroughly with water, and if irritation persists, contact a veterinarian.

• VET-STRENGTH • CLINICAL FORMULA

VETERINARIAN RECOMMENDED

CLEANSING & SOOTHING

TARGETS SKIN IRRITATION

SOOTHING ALOE VERA

ditch the itch!™

Made in the USA from US & globally sourced ingredients.